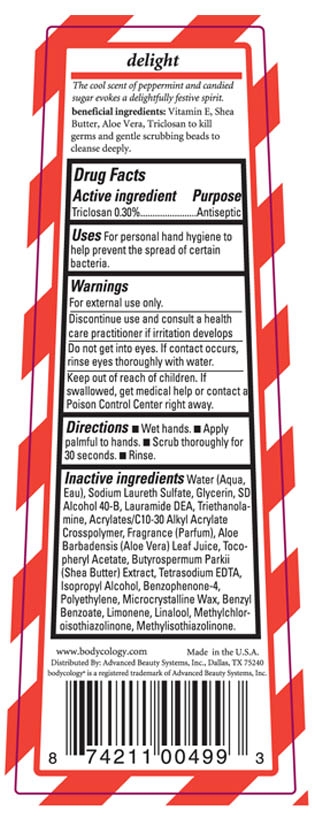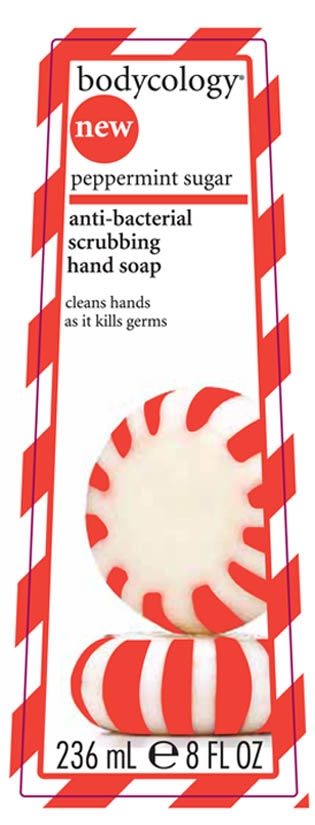 DRUG LABEL: Bodycology Peppermint Sugar anti-bacterial scrubbing hand soap
NDC: 65663-023 | Form: LIQUID
Manufacturer: American Blending and Filling
Category: otc | Type: HUMAN OTC DRUG LABEL
Date: 20100505

ACTIVE INGREDIENTS: Triclosan .30 mL/100 mL

Drug Facts

Active Ingredient

Triclosan

Purpose Antiseptic

Uses For personal hand hygiene to help prevent the spread of certain bacteria.

Warnings

For external use only

STOP USE

Discontinue use and consult a health care practitioner if irritation develops

PRECAUTIONS

Do not get into eyes. If contact occurs, rinse eyes thoroughly with water.

Keep out of reach of children. If swallowed, get medical help or contact a Poison Control Center right away.

Directions Wet hands. Apply palmful to hands. Scrub thoroughly for 30 seconds. Rinse.

INACTIVE INGREDIENT

Inactive Ingredients Water (Aqua, Eau), Sodium Laureth Sulfate, Glycerine, SD Alcohol 40B, Lauramide DEA, Triethanolamine, Acrylates/C10-30 Alkyl Acrylate Crosspolymer, Fragrance (Parfum), Aloe Barbadensis (Aloe Vera) Leaf Juice, Tocopheryl Acetate, Butyrospermum Parkii (Shea Butter) Extract, Tetrasodium EDTA, Isopropyl Alcohol, Benzophenone-4, Polyethylene, Microcrystalline Wax, Benzyl Benzoate, Limonene, Linalool, Methylchloroisothiazolinone, Methylisothaizolinone.